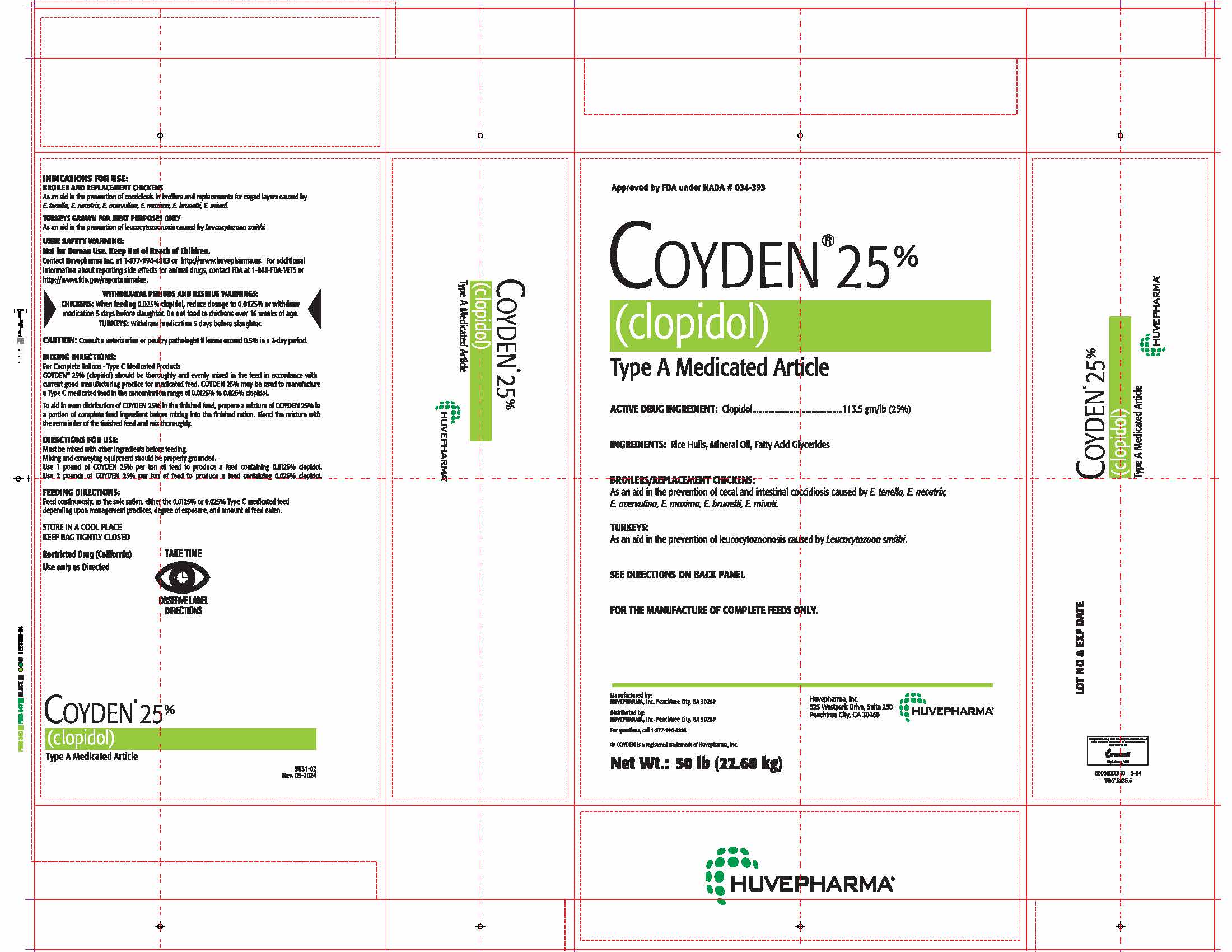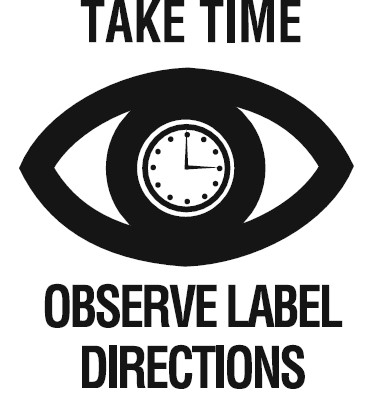 DRUG LABEL: Coyden
NDC: 23243-9568 | Form: POWDER
Manufacturer: Huvepharma, Inc.
Category: animal | Type: OTC TYPE A MEDICATED ARTICLE ANIMAL DRUG LABEL
Date: 20240508

ACTIVE INGREDIENTS: CLOPIDOL 250.2 g/1 kg
INACTIVE INGREDIENTS: MINERAL OIL; RICE BRAN

Approved by the FDA under NADA # 034-393

COYDEN® 25%
(clopidol)
Type A Medicated Article

ACTIVE INGREDIENT

ACTIVE DRUG INGREDIENT: Clopidol.................................113.5 gm/lb (25%)

INACTIVE INGREDIENT

INGREDIENTS: Rice Hulls, Mineral Oil, Fatty Acid Glycerides

INDICATIONS AND USAGE

BROILER/REPLACEMENT CHICKENS:
As an aid in the prevention of cecal and intestinal cocciodiosis caused by E. tenella, E. necatrix,
E. acervulina, E. maxima, E. brunetti, E. mivati.

TURKEYS:
As an aid in the prevention of leucocytozoonosis caused by Leucocytozoon smithi.

SEE DIRECTIONS ON BACK PANEL

FOR THE MANUFACTURE OF COMPLETE FEEDS ONLY.

Manufactured by:
HUVEPHARMA, Inc. Peachtree City, GA 30269 Huvepharma, Inc.
525 Westpark Drive, Suite 230
Distributed by: Peachtree City, GA 30269
HUVEPHARMA, Inc. Peachtree City, GA 30269

For questions, call 1-877-994-4883

® COYDEN is a registered trademark of Huvepharma, Inc.

Net Wt.: 50 lb (22.68 kg)

INDICATIONS FOR USE:
BROILER AND REPLACEMENT CHICKENS
As an aid in the prevention of coccidiosis in broilers and replacements for caged layers caused by
E. tenella, E. necatrix, E. acervulina, E. maxima, E. brunetti, E. mivati.

TURKEYS GROWN FOR MEAT PURPOSES ONLY
As an aid in the prevention of leucocytozoonosis caused by Leucocytozoon smithi.

USER SAFETY WARNING:
Not for Human Use. Keep Out of Reach of Children.
Contact Huvepharma Inc. at 1-877-994-4883 or http://www.huvepharma.us. For additional
information about reporting side effects for animal drugs, contact FDA at 1-888-FDA-VETS or
http://www.fda.gov/reportanimalae.

WITHDRAWAL PERIODS AND RESIDUE WARNINGS:
CHICKENS: When feeding 0.025% clopidol, reduce dosage to 0.0125% or withdraw
medication 5 days before slaughter. Do not feed to chickens over 16 weeks of age.
TURKEYS: Withdraw medication 5 days before slaughter.

GENERAL PRECAUTIONS

CAUTION: Consult a veterinarian or poultry pathologist if losses exceed 0.5% in a 2-day period.

DOSAGE AND ADMINISTRATION

MIXING DIRECTIONS:
For Complete Rations - Type C Medicated Products
COYDEN® 25% (clopidol) should be thoroughly and evenly mixed in the feed in accordance with
current good manufacturing practice for medicated feed. COYDEN 25% may be used to manufacture
a Type C medicated feed in the concentration range of 0.0125% to 0.025% clopidol.

To aid in even distribution of COYDEN 25% in the finished feed, prepare a mixture of COYDEN 25% in
a portion of complete feed ingredient before mixing into the finished ration. Blend the mixture with
the remainder of the finished feed and mix thoroughly.

DIRECTIONS FOR USE:
Must be mixed with other ingredients before feeding.
Mixing and conveying equipment should be properly grounded.
Use 1 pound of COYDEN 25% per ton of feed to produce a feed containing 0.0125% clopidol.
Use 2 pounds of COYDEN 25% per ton of feed to produce a feed containing 0.025% clopidol.

FEEDING DIRECTIONS:
Feed continuously, as the sole ration, either the 0.0125% or 0.025% Type C medicated feed
depending upon management practices, degree of exposure, and amount of feed eaten.

STORAGE AND HANDLING

STORE IN A COOL PLACE
KEEP BAG TIGHTLY CLOSED

USER SAFETY WARNINGS

Restricted Drug (California)
Use only as Directed